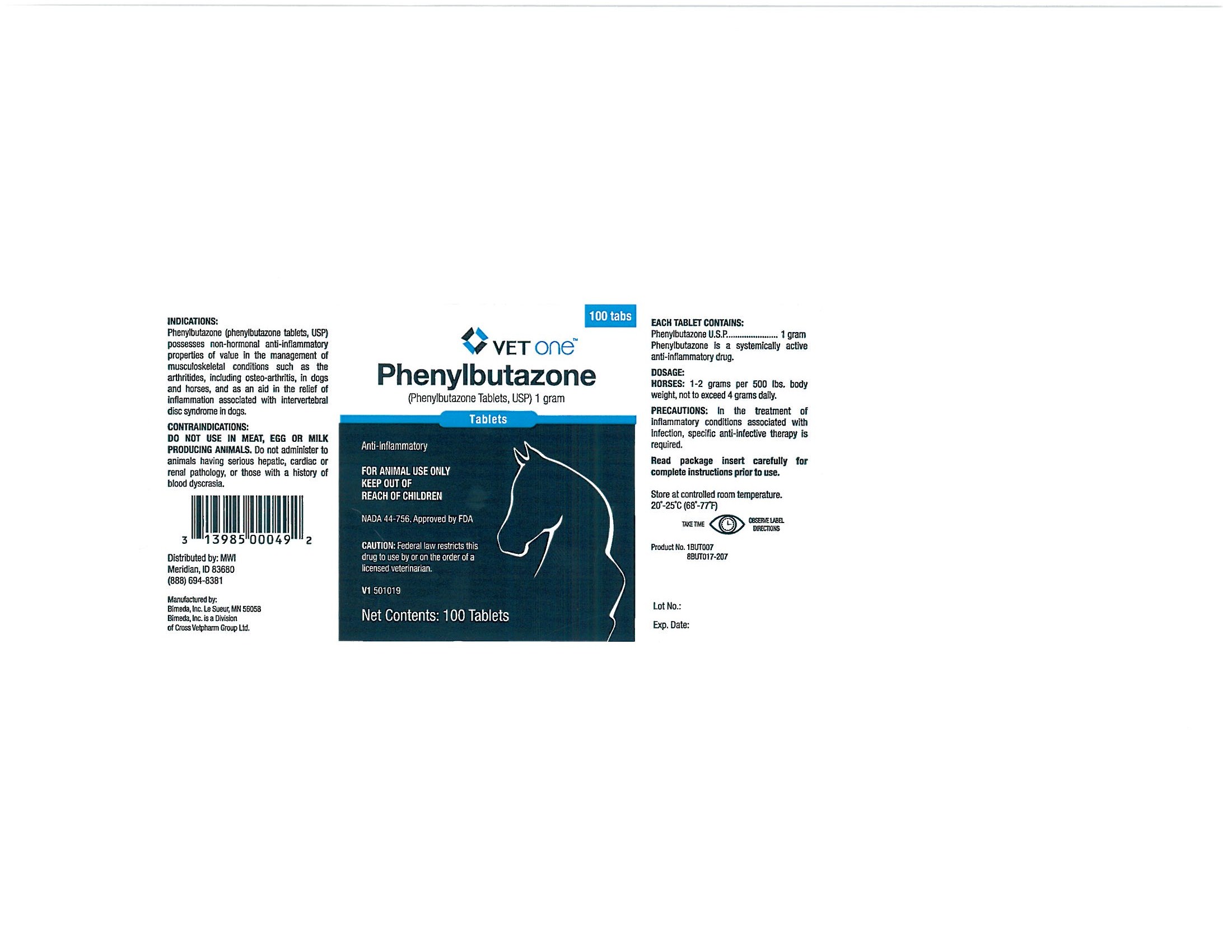 DRUG LABEL: Phenylbutazone 
NDC: 13985-019 | Form: TABLET
Manufacturer: Vet One
Category: animal | Type: PRESCRIPTION ANIMAL DRUG LABEL
Date: 20110322

ACTIVE INGREDIENTS: Phenylbutazone 1 g/3.027 g

GENERAL PRECAUTIONS

CAUTION:

Federal law restricts this drug to use by or on the order of a licensed veterinarian.

DESCRIPTION:

Phenylbutazone is a non-hormonal, anti-inflammatory agent. Chemically, it is described as 4-Butyl-1,2-diphenyl-3,5 pyrazolidinedione, a synthetic pyrazolone derivative, entirely unrelated to the steroid compounds.

INDICATIONS AND USAGE

ACTIONS AND USES:

Kuzell (1,2,3), Payne (4), Flemming (5) and Denko (6), demonstrated clinical effectiveness of phenylbutazone in acute rheumatism, gout, gouty arthritis and various other rheumatoid diseases in man. Anti-inflammatory activity has been well established by Fabre (7), Domenjoz (8), Wilhelmi (9), and Yourish (10).

Lieberman (11) reported on the effective use of phenylbutazone in the treatment of conditions of the musculoskeletal system in dogs, including posterior paralysis associated with intervertebral disc syndrome, fractures, arthritis and injuries to the limbs and joints. Joshua (12) observed objective improvement without toxicity following long-term therapy of two aged arthritic dogs. Ogilvie and Sutter (13) reported rapid response to phenylbutazone therapy in a review of 19 clinical cases including posterior paralysis, posterior weakness, arthritis, rheumatism and other conditions associated with lameness and musculoskeletal weakness.

Camberos (14) reported favorable results with phenylbutazone following intermittent treatment of thoroughbred horses and arthritis and chronic arthrosis (e.g. osteoarthritis of medical and distal bones of the hock, arthritis of the stifle and hip, arthrosis of the spine and generalized arthritis). Results were less favorable in cases of traumatism, muscle rupture, strains and inflammatory conditions of the third phalanx. Sutter (15) reported favorable responses in chronic equine arthritis, fair results in a severely bruised mare, and poor results in two cases where the condition was limited to the third phalanx.

INDICATIONS:

Phenylbutazone possesses non-hormonal, anti-inflammatory activity of value in the management of musculoskeletal conditions in dogs and horses such as the arthritides, including osteoarthritis, and as an aid in the relief of inflammation associated with intervertebral disc syndrome in dogs.

CONTRAINDICATIONS:

Phenylbutazone should not be administered to animals with serious hepatic, renal or cardiac pathology, or those with a history of blood dyscrasia.

WARNING:

PHENYLBUTAZONE SHOULD NOT BE ADMINISTERED TO MEAT, EGG OR MILK PRODUCING ANIMALS BECAUSE THE STATUS OF RESIDUES OF DRUG REMAINING IN EDIBLE TISSUES HAS NOT BEEN DETERMINED.

HAZARDS AND PRECAUTIONS:

1. Use with caution in animals with a history of drug allergy.

2. Stop medication at the first sign of gastrointestinal upset, jaundice or blood dyscrasia. Authenticated cases of agranulocytosis associated with phenylbutazone have occured in man. Phenylbutazone induced blood dyscrasias have been reported in dogs. Throbocytopenia and leukopenia are early manifestations followed by nonregenerative anemia. The occurrence of this reaction is not dose depended and is unpredictable. To guard against this possibility, conduct routine blood counts at not more than 7 day intervals during the early course of therapy, and at intervals of not more than 14 days throughout the course of therapy. Any significant fall in the total white count, relative decrease in granulocytes or black or tarry stools should be regarded as a signal for immediate cessation of therapy and institution of appropriate treatment.

3. When treating inflammatory conditions associated with infection, specific anti-infective therapy is required.

4. Response to phenylbutazone therapy is prompt, usually occurring within 24 hours. If no significant clinical response is evident after 5 days of therapy, re-evaluate diagnosis and therapeutic regimen.

DOSAGE-DOGS:

ORALLY

20 mg per pound body weight (100 mg/5 lbs.) daily in 3 divided doses, not to exceed 800 mg daily regardless of body weight.

DOSAGE-HORSES:

ORALLY 1-2 grams per 500 lbs. body weight, not to exceed 4 grams daily.

ADMINISTRATION:

1. Use a relatively high dose for the first 48 hours, then reduce gradually to a maintenance dose. Maintain lowest dose capable of producing the desired clinical response.

2. In many cases tablets may be crushed and given with feed. Reduce the dosage as symptoms regress. In some cases treatment may be given only when symptoms appear with no need for continuous medication.

3. In animals, phenylbutazone is largely metabolized in 8 hours. It is recommended that a third of the daily dose be administered at 8 hour intervals.

4. Many chronic conditions will respond to phenylbutazone therapy but discontinuance of treatment may result in the recurrence of symptoms.

STORAGE:

Store at controlled room temperature, 20o-25o C (68o-77o F).

HOW SUPPLIED:

BUTATRON (Phenylbutazone Tablets, U.S.P.) are supplied in the following tablet concentrations and package sizes:

100 mg tablets.......................Bottles of 1000 tablets

1 gram tablets........................Bottles of 100 tablets

REFERENCES:

1. Kuzell, W.C., Schaffarzick, R.W., Naugler, W.G., Mankle, E.A., A.M.A. Arch. Int. Med 92:646,1953.

2. Kuzzel, W.C., Schaffarzick, R.W., Brown, B., Mankle, E.A., Jour. Amer. Med. Assoc. 149:729, 1952.

3. Kuzell, W.C., Schaffarzick, R.W., Cal. Med 77:319, 1952.

4. Payne, R.W., Shetlar, M.R., Farr, C., Hellbaum, A.A., and Ishmael, W.K.T., J. Lab. Clin. Med. 45:331, 1955.

5. Flemming, J. and Will, G., Ann. Rheumat. Dis. 12:95, 1953.

6. Denko, C.W., Ruml, D., Amer. Practit. 6:1865, 1955.

7. Fabre, J. and Bergen, A., Semaine Hop. (Paris) 31:87, 1955.

8. Domenjoz, R., Theobald, W. and Morsdorf, K., Arzneimittel-Forsch. 5:488, 1955.

9. Wilhelmi, G. and Pulver, R., Arzneimittel-Forsch. 5:221, 1955.

10. Yourish, N., Paton, B., Brodie, B.B. and Burns, J.J., A.M.A. Arch. Ophth. 53:264, 1955.

11. Lieberman, L.L., Jour. A.V.M.A. 125:128, 1954.

12. Joshua, J.O., Vet. Rec. 68:60 (Jan. 21), 1956.

13. Ogilvie, F.B. and Sutter, M.B., Vet. Med 52:492-494, 1957.

14. Camberos, H.R., Rev. Med. Vet. (Buenos Aires) 38:9, 1956.

15. Sutter, M.D., Vet. Med. 58:83 (Feb.), 1958.

GENERAL PRECAUTIONS

FOR ANIMAL USE ONLY

KEEP OUT OF REACH OF CHILDREN

PACKAGE LABEL

Phenylbutazone

(Phenylbutazone Tablets, USP) 1 gram

Tablets

Anti-Inflammatory

FOR ANIMAL USE ONLY

KEEP OUT OF REACH OF CHILDREN

NADA 44-756, Approved by FDA

CAUTION: Federal law restricts this drug to use by or on the order of a licensed veterinarian.